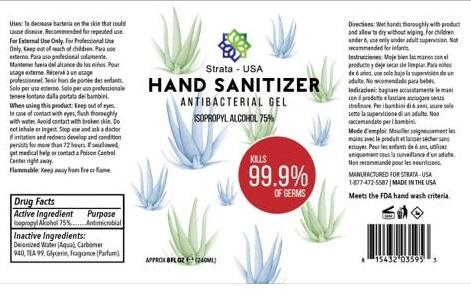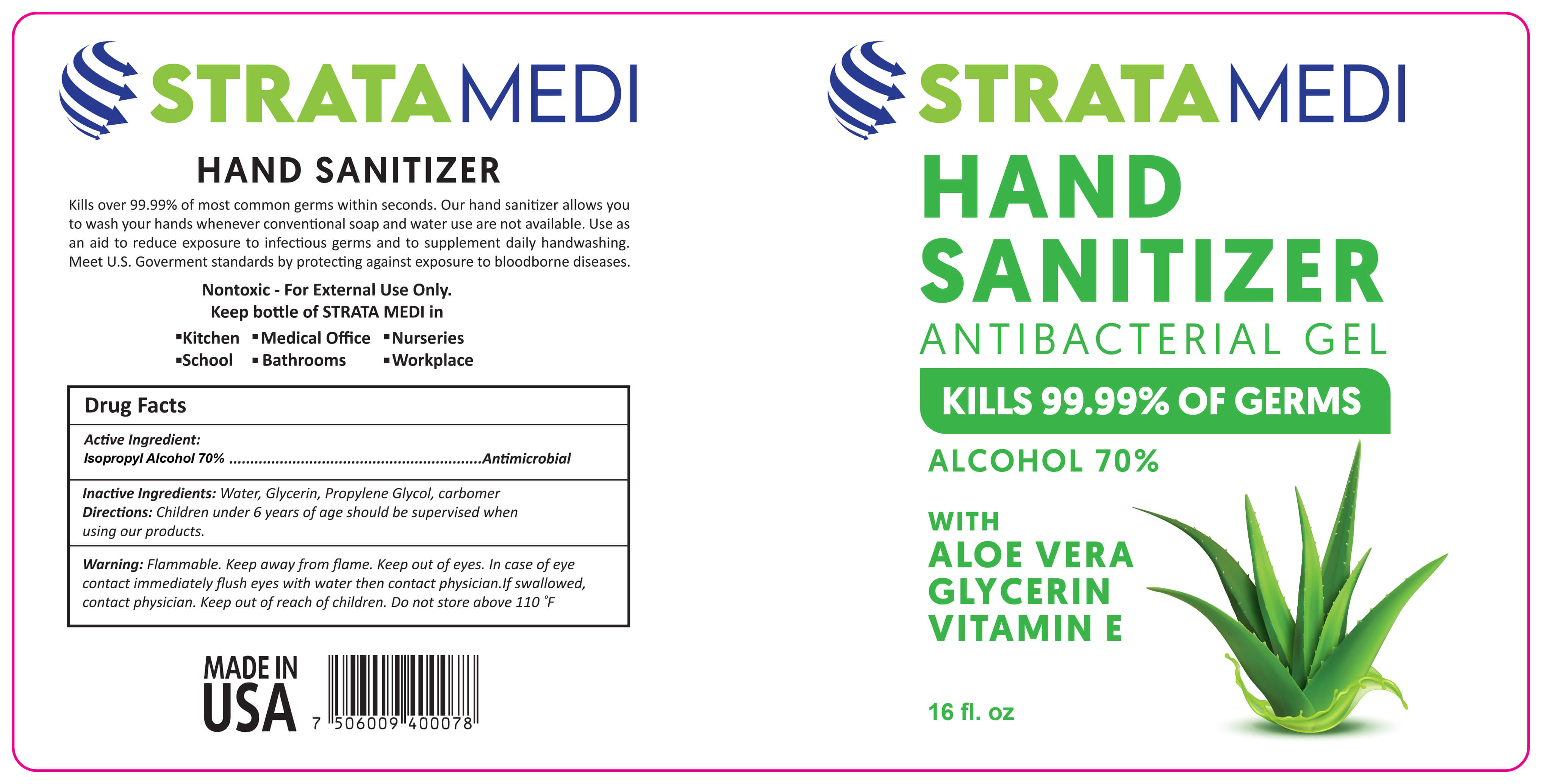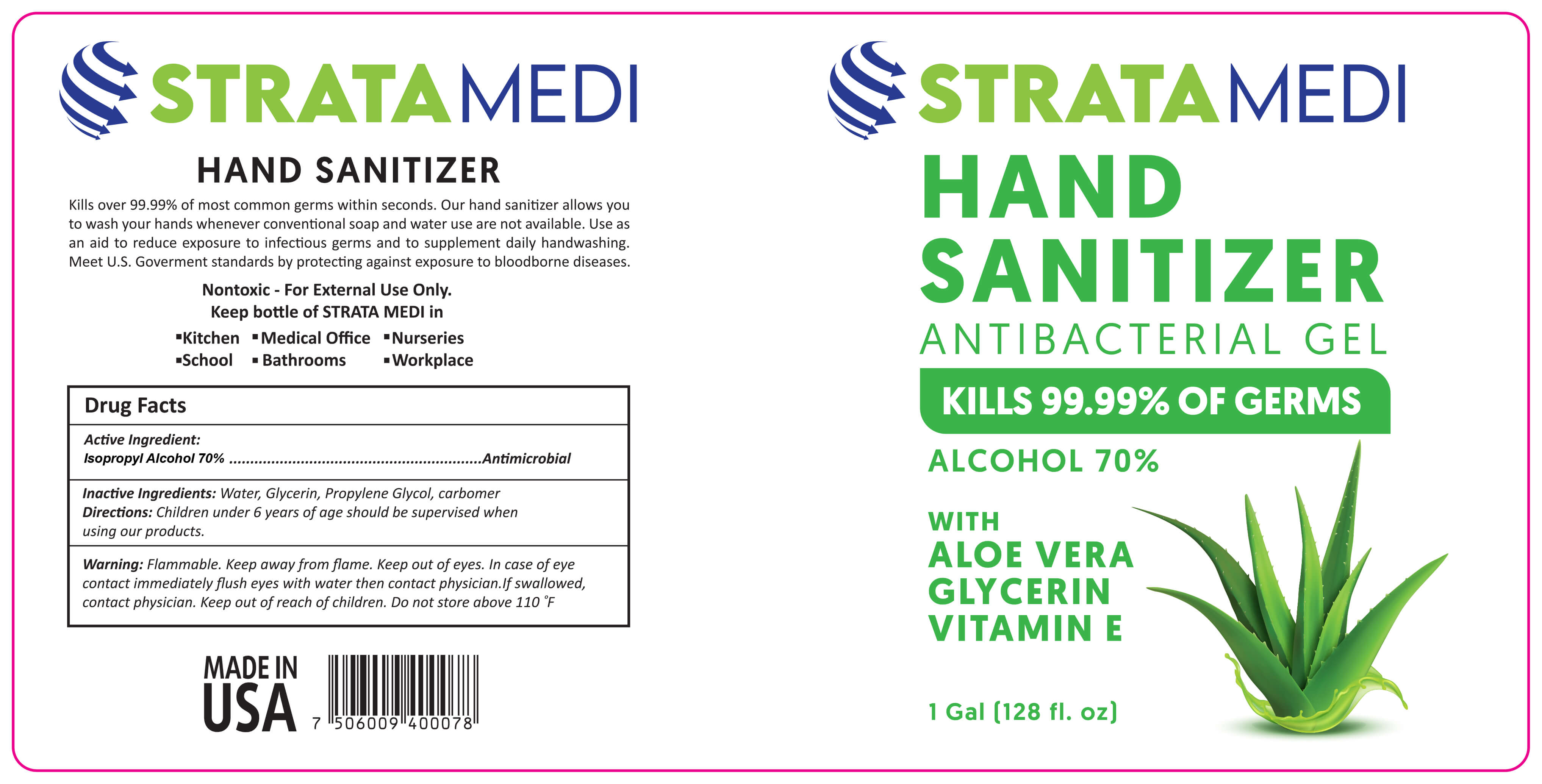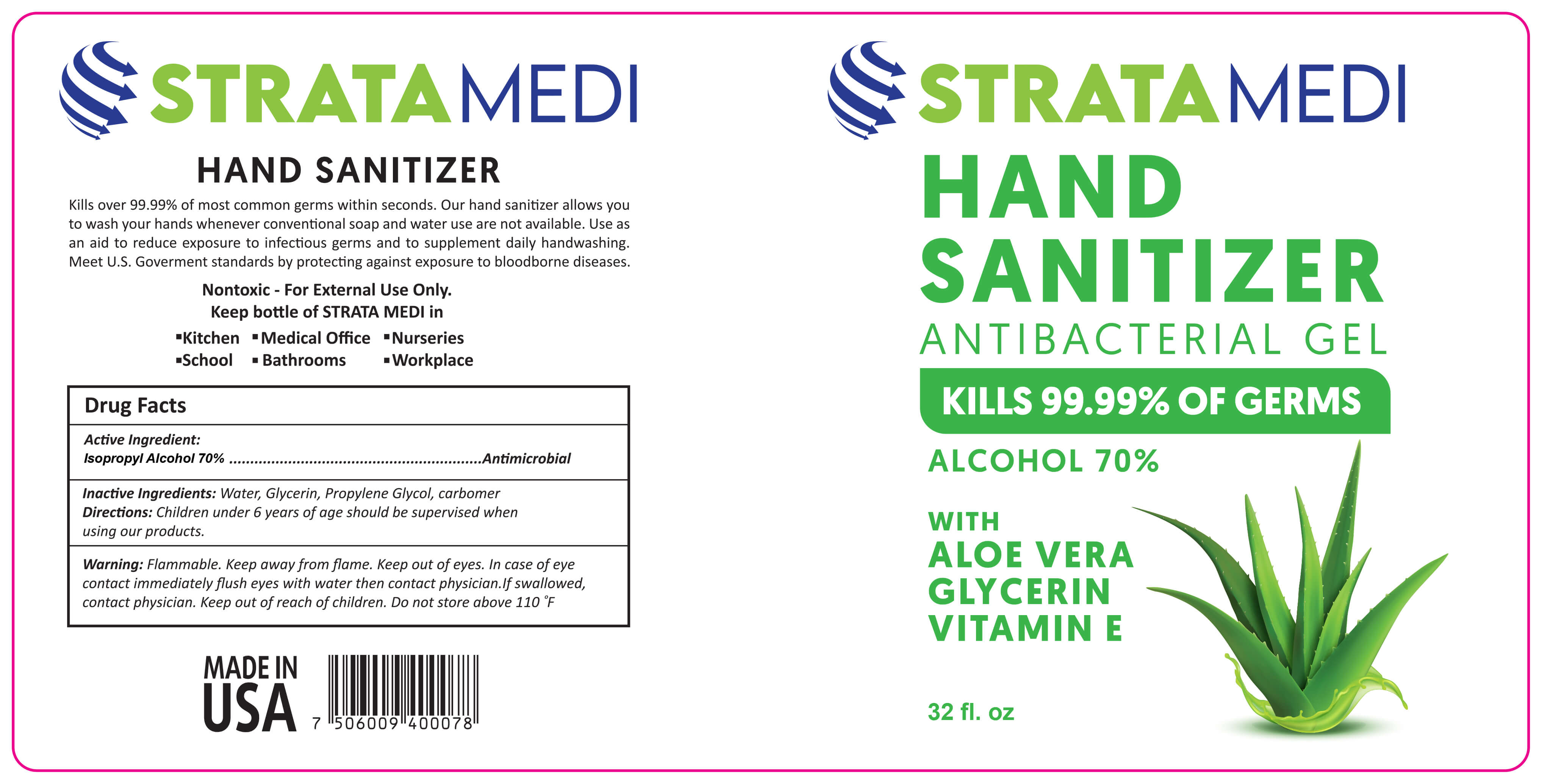 DRUG LABEL: StrataMedi Hand Sanitizer
NDC: 77004-201 | Form: GEL
Manufacturer: Strata USA LLC
Category: otc | Type: HUMAN OTC DRUG LABEL
Date: 20200825

ACTIVE INGREDIENTS: ISOPROPYL ALCOHOL 70 mL/100 mL
INACTIVE INGREDIENTS: WATER 24 mL/100 mL; CARBOMER 940 0.3 mL/100 mL; TROLAMINE 0.1 mL/100 mL; ALOE VERA LEAF 0.2 mL/100 mL; GLYCERIN 0.1 mL/100 mL

Impulse Antibacterial Hand Sanitizer with Isopropyl Alcohol 8oz, 16 oz 32 oz 1 Gall Gel

ACTIVE INGREDIENT

Isopropyl Alcohol 70%......................................Antimicrobial

Inactive Ingredients: Water, Glycerin, Propylene Glycol, Carbomer

DOSAGE AND ADMINISTRATION

Our hand sanitizer allows you to wash your hands whenever conventional soal and water use are not available

INDICATIONS AND USAGE

Children under 6 years of age should be supervised when using our products

Keep out of reach of children

WARNINGS

Flammable. Keep away from flame. Keep out of eyes. In case of eye contact, immediately flush eyes with water then contact physician. if swallowed, contact physician. Keep out of reach of children. Do not store above 110° F

PURPOSE

Kills over 99.99% of most common gerns with seconds. our hand sanitizer allows you to wash yur hands whenever conventional soap and water are not available. use as an aid to reduce exposure to infectious germs and to supplement daily handwashing. meet US government standards by protecting against exposre to bloodborne diseases.